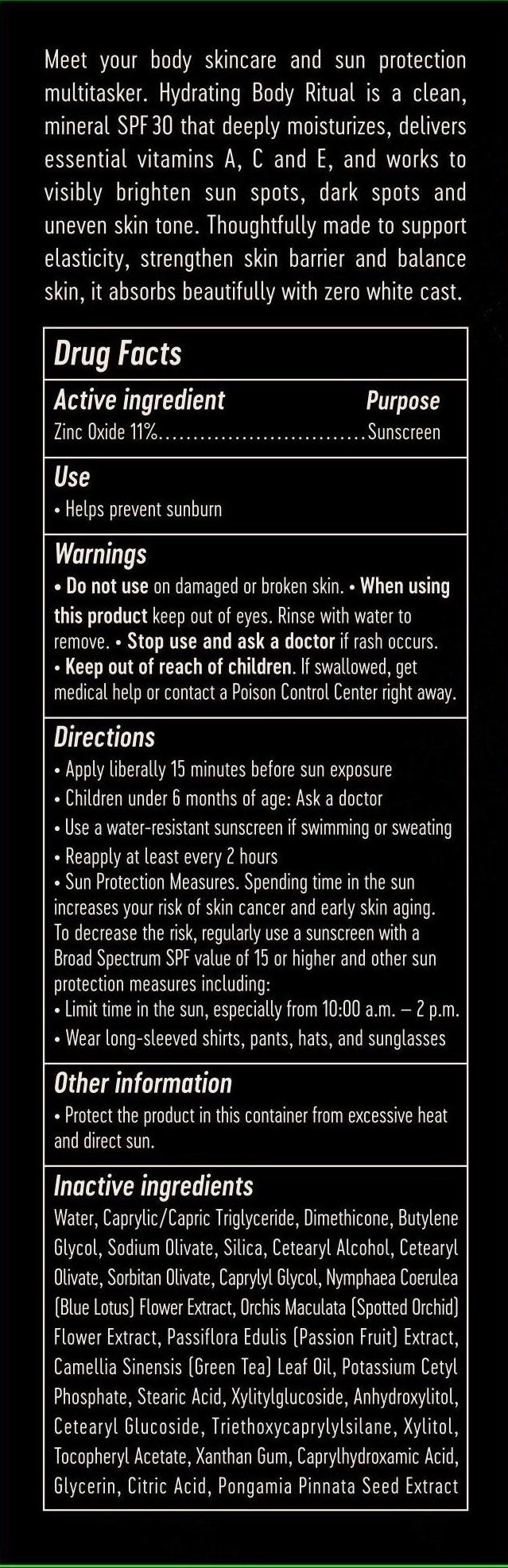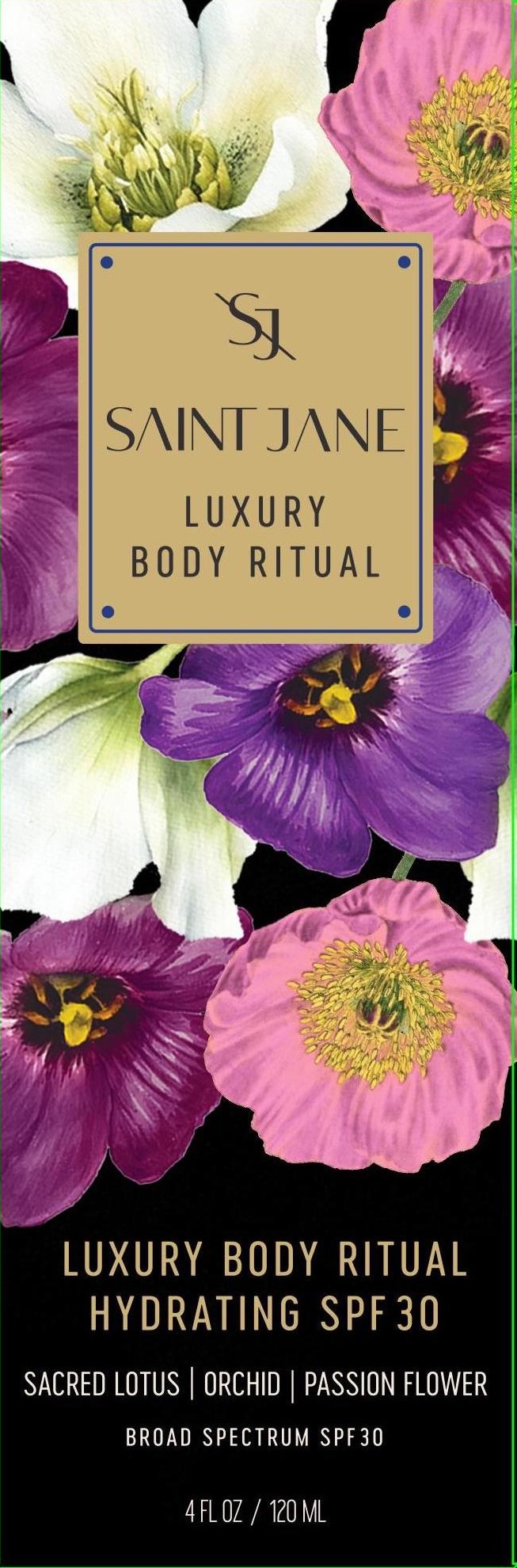 DRUG LABEL: LUXURY BODY RITUAL
NDC: 82404-102 | Form: LOTION
Manufacturer: JANE STREET LLC
Category: otc | Type: HUMAN OTC DRUG LABEL
Date: 20260112

ACTIVE INGREDIENTS: ZINC OXIDE 11 g/100 mL
INACTIVE INGREDIENTS: CITRIC ACID; PONGAMIA PINNATA SEED; SODIUM OLIVATE; DACTYLORHIZA MACULATA FLOWER; DIMETHICONE; NYMPHAEA CAERULEA FLOWER; SORBITAN OLIVATE; BUTYLENE GLYCOL; WATER; MEDIUM-CHAIN TRIGLYCERIDES; CETOSTEARYL ALCOHOL; .ALPHA.-TOCOPHEROL ACETATE; CETEARYL OLIVATE; CETEARYL GLUCOSIDE; XANTHAN GUM; GREEN TEA LEAF; TRIETHOXYCAPRYLYLSILANE; CAPRYLHYDROXAMIC ACID; CAPRYLYL GLYCOL; STEARIC ACID; XYLITOL; XYLITYLGLUCOSIDE; ANHYDROXYLITOL; PASSIFLORA EDULIS FRUIT; SILICON DIOXIDE; POTASSIUM CETYL PHOSPHATE; GLYCERIN

SJ (as PLD): LUXURY BODY RITUAL SPF30 (82404-102)

ACTIVE INGREDIENT

ZINC OXIDE 11%

PURPOSE

SUNSCREEN

USE

HELPS PREVENT SUNBURN

WARNINGS

- FOR EXTERNAL USE ONLY.

- DO NOT USE ON DAMAGED OR BROKEN SKIN.

WHEN USING THIS PRODUCT KEEP OUT OF EYES. RINSE WITH WATER TO REMOVE.

- STOP USE AND ASK A DOCTOR IF RASH OCCURS.

- KEEP OUT OF REACH OF CHILDREN. IF SWALLOWED, GET MEDICAL HELP OR CONTACT A POISON CONTROL CENTER RIGHT AWAY.

DIRECTIONS

- APPLY LIBERALLY 15 MINUTES BEFORE SUN EXPOSURE.
- CHILDREN UNDER 6 MONTHS OF AGE: ASK A DOCTOR.
- USE A WATER-RESISTANT SUNSCREEN IF SWIMMING OR SWEATING.
- REAPPLY AT LEAST EVERY 2 HOURS.
- SUN PROTECTION MEASURES: SPENDING TIME IN THE SUN INCREASES YOUR RISK OF SKIN CANCER AND EARLY SKIN AGING. TO DECREASE THIS RISK, REGULARLY USE A SUNSCREEN WITH A BROAD SPECTRUM SPF VALUE OF 15 OR HIGHER AND OTHER SUN PROTECTION MEASURES INCLUDING:
- LIMIT TIME IN THE SUN, ESPECIALLY FROM 10 A.M. - 2 P.M.
- WEAR LONG-SLEEVED SHIRTS, PANTS, HATS, AND SUNGLASSES.

OTHER INFORMATION

- PROTECT THE PRODUCT IN THIS CONTAINER FROM EXCESSIVE HEAT AND DIRECT SUN.

INACTIVE INGREDIENTS

Water, Caprylic/Capric Triglyceride, Dimethicone, Butylene Glycol, Sodium Olivate, Silica, Cetearyl Alcohol, Cetearyl Olivate, Sorbitan Olivate, Caprylyl Glycol, Nymphaea Coerulea (Blue Lotus) Flower Extract, Orchis Maculata (Spotted Orchid) Flower Extract, Passiflora Edulis (Passion Fruit) Extract, Camellia Sinensis (Green Tea) Leaf Oil, Potassium Cetyl Phosphate, Stearic Acid, Xylitylglucoside, Anhydroxylitol, Cetearyl Glucoside, Triethoxycaprylylsilane, Xylitol, Tocopheryl Acetate, Xanthan Gum, Caprylhydroxamic Acid, Glycerin, Citric Acid, Pongamia Pinnata Seed Extract